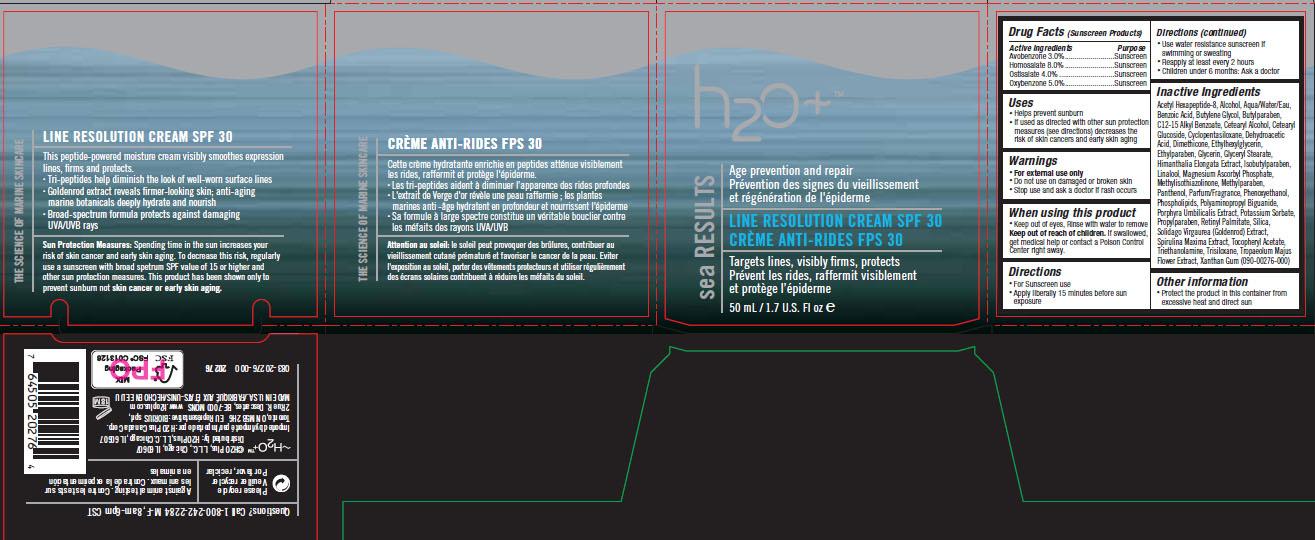 DRUG LABEL: Sea Results Line Resolution
NDC: 65903-276 | Form: CREAM
Manufacturer: H2O PLUS
Category: otc | Type: HUMAN OTC DRUG LABEL
Date: 20110929

ACTIVE INGREDIENTS: Avobenzone 3 mL/100 mL; Homosalate 8 mL/100 mL; Octisalate 4 mL/100 mL; Oxybenzone 5 mL/100 mL
INACTIVE INGREDIENTS: ACETYL HEXAPEPTIDE-3; ALCOHOL; WATER; BENZOIC ACID; BUTYLENE GLYCOL; BUTYLPARABEN; ALKYL (C12-15) BENZOATE; CETOSTEARYL ALCOHOL; C12-20 ALKYL GLUCOSIDE; CYCLOMETHICONE 5; DEHYDROACETIC ACID; DIMETHICONE; ETHYLHEXYLGLYCERIN; ETHYLPARABEN; GLYCERIN; GLYCERYL MONOSTEARATE; HIMANTHALIA ELONGATA; ISOBUTYLPARABEN; LINALOOL, (+)-; MAGNESIUM ASCORBYL PHOSPHATE; METHYLISOTHIAZOLINONE; METHYLPARABEN; PANTHENOL; PHENOXYETHANOL; LECITHIN, SOYBEAN; PORPHYRA UMBILICALIS; POTASSIUM SORBATE; PROPYLPARABEN; VITAMIN A PALMITATE; SILICON DIOXIDE; SOLIDAGO VIRGAUREA FLOWERING TOP; SPIRULINA MAXIMA; .ALPHA.-TOCOPHEROL ACETATE, DL-; TRIETHANOLAMINE HYDROCHLORIDE; TRISILOXANE; TROPAEOLUM MAJUS; XANTHAN GUM

Drug Facts

ACTIVE INGREDIENT

Avobenzone 3.0%
Homosalate 8.0%
Octisalate 4.0%
Oxybenzone 5.0%

PURPOSE

Sunscreen
Sunscreen
Sunscreen
Sunscreen

PURPOSE

• Helps prevent sunburn
• If used as directed with other sun protection measures
(see directions) decreases the risk of skin cancers and early skin aging

WARNINGS

• For external use only • Do not use on damaged or broken skin
• Stop use and ask a doctor if rash occurs

• Keep out of eyes, Rinse with water to remove. Keep out of reach of children.
If swallowed, get medical help or contact a Poison Control Center right away

DOSAGE AND ADMINISTRATION

• For Sunscreen use
• Apply liberally 15 minutes before sun exposure
• Use water resistance sunscreen if swimming or sweating
• Reapply at least every 2 hours
• Children under 6 months: Ask a doctor

STORAGE AND HANDLING

Protect the product in this container from excessive heat
and direct sun

INACTIVE INGREDIENT

Acetyl Hexapeptide-8, Alcohol, Aqua/Water/Eau,
Benzoic Acid, Butylene Glycol, Butylparaben,
C12-15 Alkyl Benzoate, Cetearyl Alcohol, Cetearyl
Glucoside, Cyclopentasiloxane, Dehydroacetic
Acid, Dimethicone, Ethylhexylglycerin,
Ethylparaben, Glycerin, Glyceryl Stearate,
Himanthalia Elongata Extract, Isobutylparaben,
Linalool, Magnesium Ascorbyl Phosphate,
Methylisothiazolinone, Methylparaben,
Panthenol, Parfum/Fragrance, Phenoxyethanol,
Phospholipids, Polyaminopropyl Biguanide,
Porphyra Umbilicalis Extract, Potassium Sorbate,
Propylparaben, Retinyl Palmitate, Silica,
Solidago Virgaurea (Goldenrod) Extract,
Spirulina Maxima Extract, Tocopheryl Acetate,
Triethanolamine, Trisiloxane, Tropaeolum Majus
Flower Extract, Xanthan Gum

Image of Label Carton srlr276.jpg